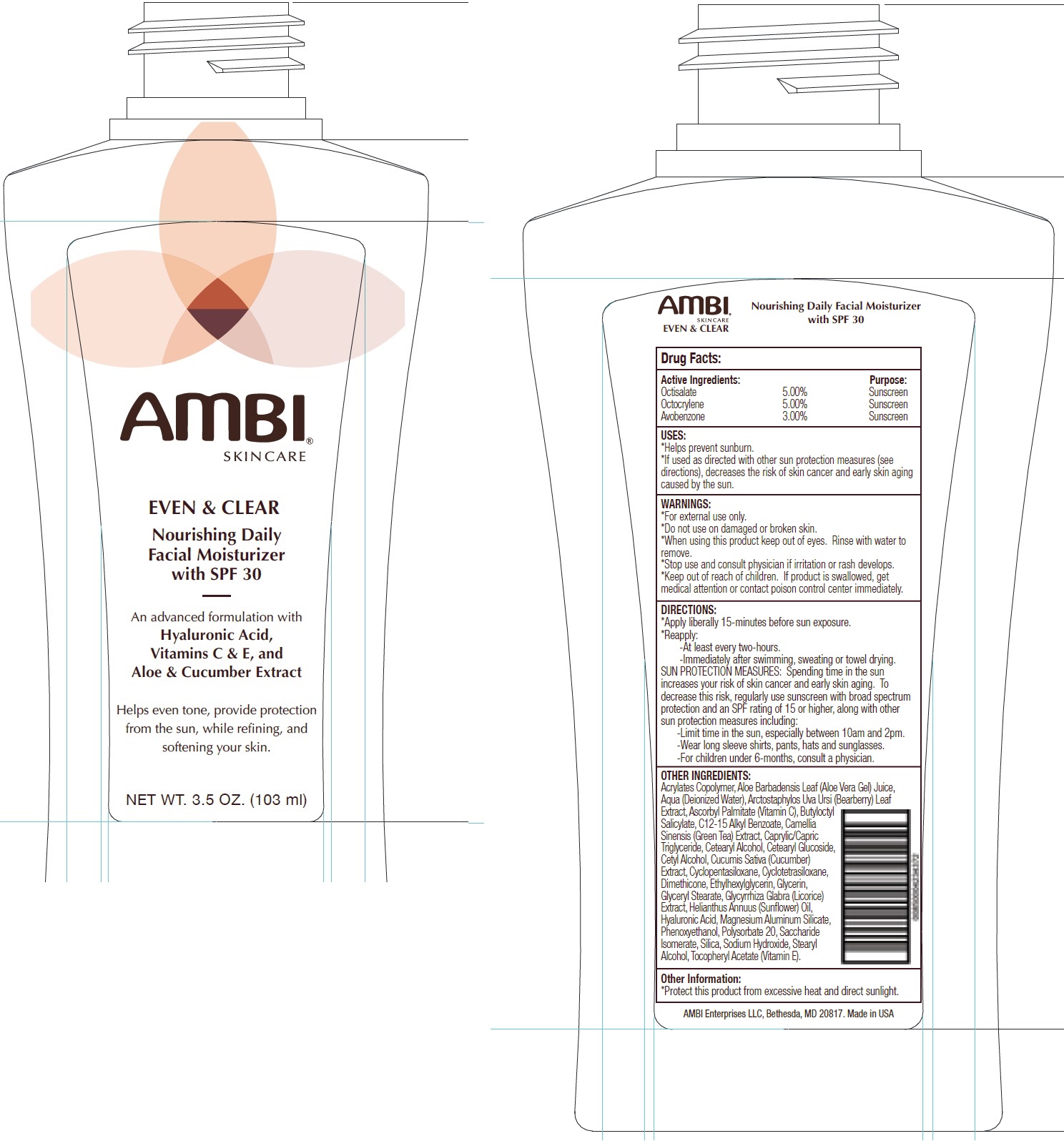 DRUG LABEL: AMBI SKINCARE Even and Clear Daily Facial Moisturizer SPF 30
NDC: 73453-073 | Form: CREAM
Manufacturer: AMBI Enterprises LLC
Category: otc | Type: HUMAN OTC DRUG LABEL
Date: 20250724

ACTIVE INGREDIENTS: OCTISALATE 50 mg/1 mL; OCTOCRYLENE 50 mg/1 mL; AVOBENZONE 30 mg/1 mL
INACTIVE INGREDIENTS: BUTYL ACRYLATE/METHYL METHACRYLATE/METHACRYLIC ACID COPOLYMER (18000 MW); ALOE VERA LEAF; WATER; ARCTOSTAPHYLOS UVA-URSI LEAF; ASCORBYL PALMITATE; BUTYLOCTYL SALICYLATE; ALKYL (C12-15) BENZOATE; GREEN TEA LEAF; MEDIUM-CHAIN TRIGLYCERIDES; CETOSTEARYL ALCOHOL; CETEARYL GLUCOSIDE; CETYL ALCOHOL; CUCUMBER; CYCLOMETHICONE 5; CYCLOMETHICONE 4; DIMETHICONE; ETHYLHEXYLGLYCERIN; GLYCERIN; GLYCERYL MONOSTEARATE; GLYCYRRHIZA GLABRA; HELIANTHUS ANNUUS FLOWERING TOP; HYALURONIC ACID; MAGNESIUM ALUMINUM SILICATE; PHENOXYETHANOL; POLYSORBATE 20; SACCHARIDE ISOMERATE; SILICON DIOXIDE; SODIUM HYDROXIDE; STEARYL ALCOHOL; .ALPHA.-TOCOPHEROL ACETATE

AMBI SKINCARE Even & Clear Daily Facial Moisturizer SPF-30

Active Ingredients:

Octisalate 5.00%

Octocrylene 5.00%

Avobenzone 3.00%

Purpose:

Sunscreen

USES:

- Helps prevent sunburn.
- If used as directed with other sun protection measures (see directions), decreases the risk of skin cancer and early skin aging caused by the sun.

WARNINGS:

For external use only.

Do not use on

damaged or broken skin.

When using this product

keep out of eyes. Rinse with water to remove.

Stop use and consult physician

if irritation or rash develops.

Keep out of reach of children.

If product is swallowed, get medical attention or contact poison control center immediately.

DIRECTIONS:

- Apply liberally 15-minutes before sun exposure.
- Reapply:

-At least every two-hours. -Immediately after swimming, sweating or towel drying. SUN PROTECTION MEASURES: Spending time in the sun increases your risk of skin cancer and early skin aging. To decrease this risk, regularly use sunscreen with broad spectrum protection and an SPF rating of 15 or higher, along with other sun protection measures including: -Limit time in the sun, especially between 10am and 2pm. -Wear long sleeve shirts, pants, hats and sunglasses. -For children under 6-months, consult a physician.

OTHER INGREDIENTS:

Acrylates Copolymer, Aloe Barbadensis Leaf (Aloe Vera Gel) Juice, Aqua (Deionized Water), Arctostaphylos Uva Ursi (Bearberry) Leaf Extract, Ascorbyl Palmitate (Vitamin C), Butyloctyl Salicylate, C12-15 Alkyl Benzoate, Camellia Sinensis (Green Tea) Extract, Caprylic/Capric Triglyceride, Cetearyl Alcohol, Cetearyl Glucoside, Cetyl Alcohol, Cucumis Sativa (Cucumber) Extract, Cyclopentasiloxane, Cyclotetrasiloxane, Dimethicone, Ethylhexylglycerin, Glycerin, Glyceryl Stearate, Glycyrrhiza Glabra (Licorice) Extract, Helianthus Annuus (Sunflower) Oil, Hyaluronic Acid, Magnesium Aluminum Silicate, Phenoxyethanol, Polysorbate 20, Saccharide Isomerate, Silica, Sodium Hydroxide, Stearyl Alcohol, Tocopheryl Acetate (Vitamin E).

Other Information:

* Protect this product from excessive heat and direct sunlight.